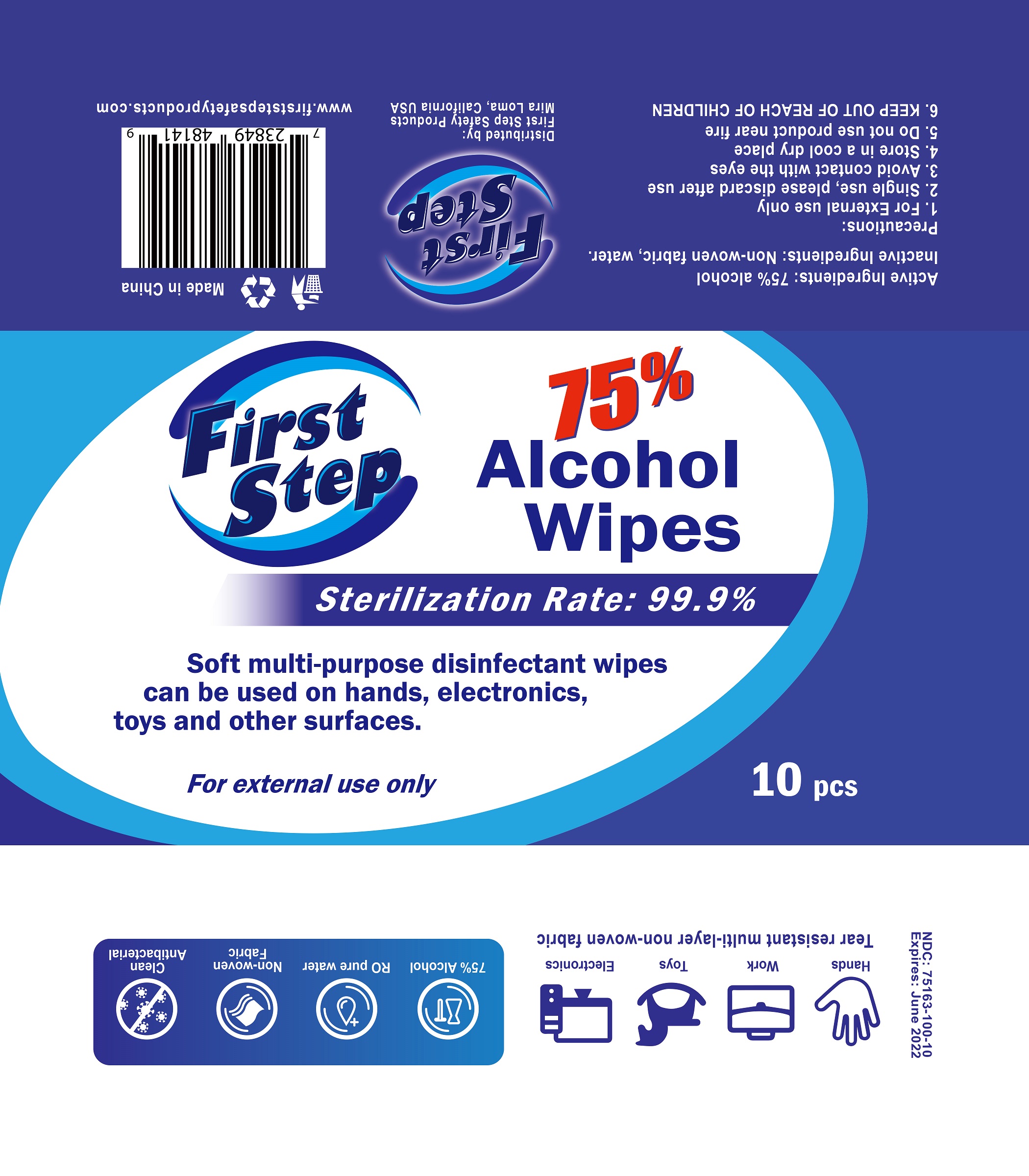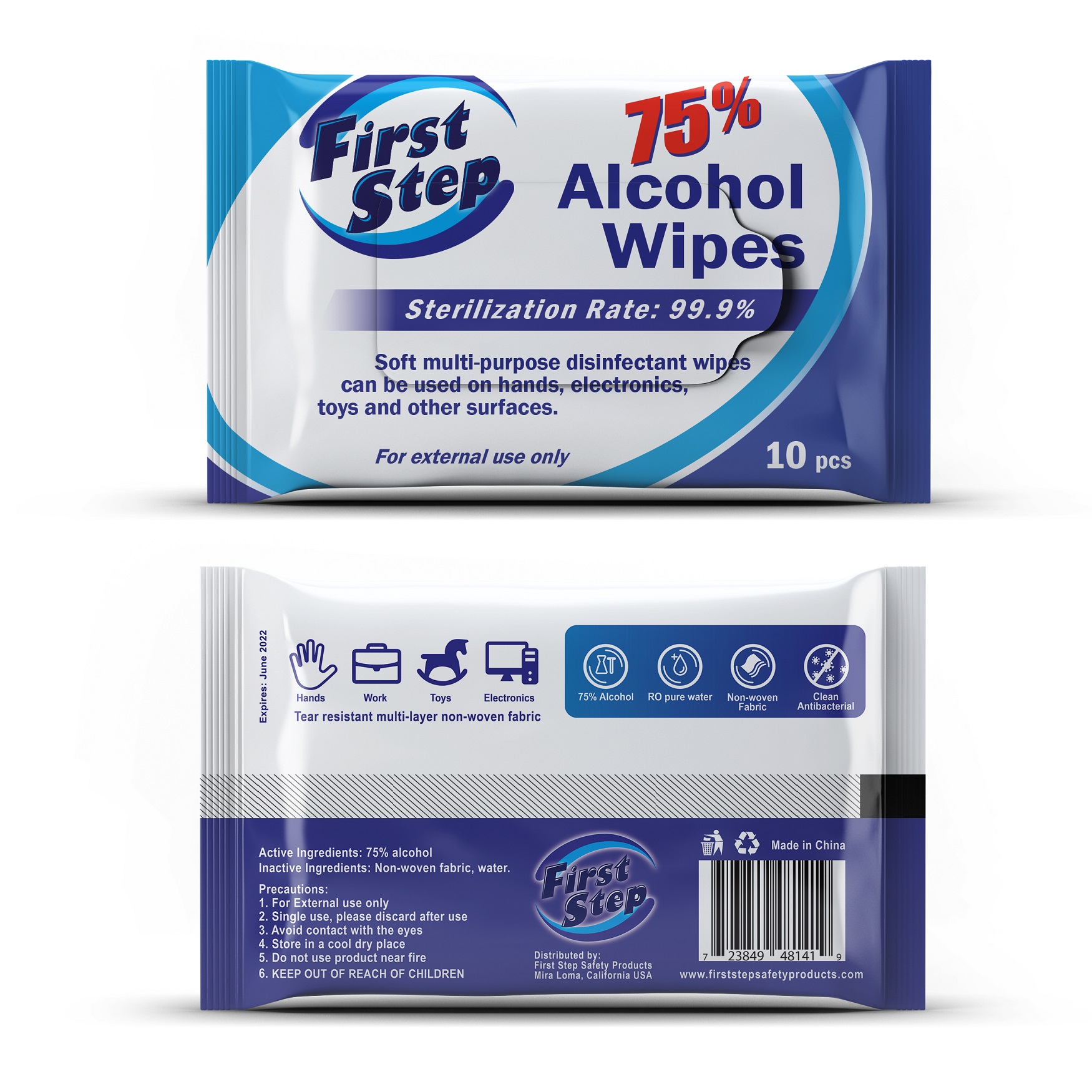 DRUG LABEL: ALCOHOL DISINFECTANT WIPES
NDC: 79195-004 | Form: CLOTH
Manufacturer: First Step Safety Products Corporation
Category: otc | Type: HUMAN OTC DRUG LABEL
Date: 20200705

ACTIVE INGREDIENTS: ALCOHOL 27.75 mL/37 1
INACTIVE INGREDIENTS: WATER

79195-004 10 CLOTH FIRST STEP BY jianhe

Active Ingredient(s)

Alcohol 75% v/v. Purpose: Antiseptic

Purpose

Disinfection
Sterilization
No Rinseing

Use

Open the cover whenusing, tear of the adhesive tape, can be exracteduse. use Afer, please fimely reduce the adhesive paste and close the cover to avoid inemal moisure eaporation.

Warnings

1. This product is only for daily use and should be stored in a cool and sealed place.
2. For extemal use only. If you find any skin discomfort or sensitivity, please stop using immediately.
3. wipe the entryable items to be used after vlatilization;
4. This product cannot be dissolved. Please do not throw it into the toilt.
5. Iflammables, do not go near the source of fire.

6.For external use only. Flammable. Keep away from heat or flame

Do not use

- in children less than 2 months of age
- on open skin wounds

When using this product keep out of eyes, ears, and mouth. In case of contact with eyes, rinse eyes thoroughly with water.
Stop use and ask a doctor if irritation or rash occurs. These may be signs of a serious condition.
Keep out of reach of children. If swallowed, get medical help or contact a Poison Control Center right away.

Stop use and ask a doctor if irritation or rash occurs. These may be signs of a serious condition.

Keep out of reach of children. If swallowed, get medical help or contact a Poison Control Center right away.

Directions

- Place enough product on hands to cover all surfaces. Rub hands together until dry.
- Supervise children under 6 years of age when using this product to avoid swallowing.

Other information

- Store between 15-30C (59-86F)
- Avoid freezing and excessive heat above 40C (104F)

Inactive ingredients

purified water USP

Package Label - Principal Display Panel

10 CLOTH IN 1 BAG NDC:79195-004-01